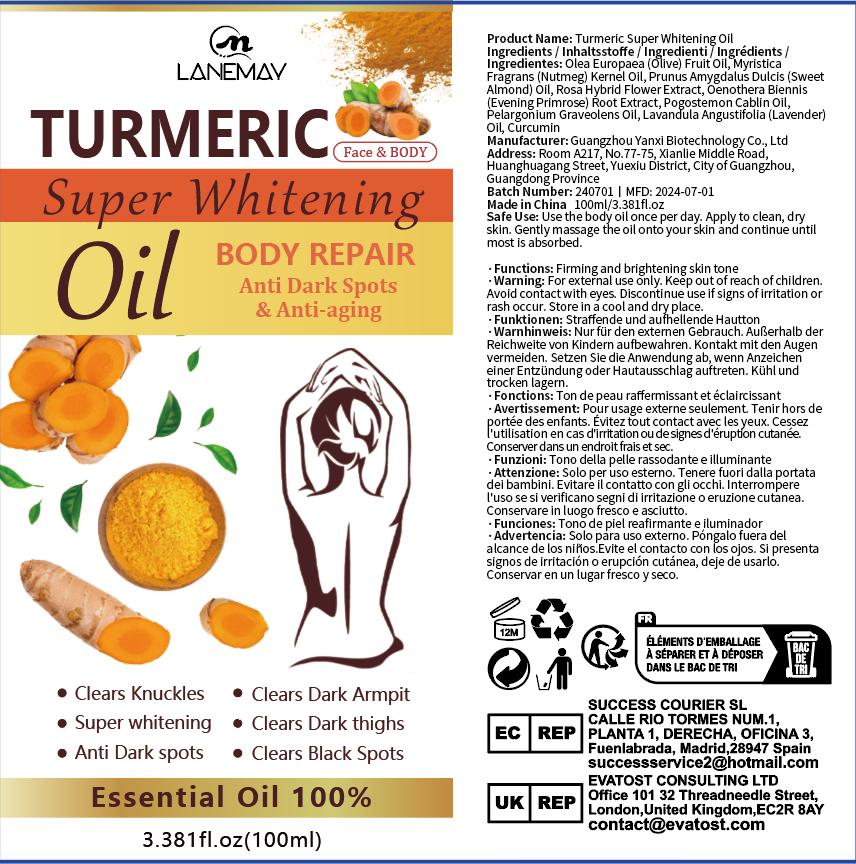 DRUG LABEL: Turmeric Super Whitening Oil
NDC: 84025-196 | Form: OIL
Manufacturer: Guangzhou Yanxi Biotechnology Co., Ltd
Category: otc | Type: HUMAN OTC DRUG LABEL
Date: 20240929

ACTIVE INGREDIENTS: CURCUMIN 5 mg/100 mL
INACTIVE INGREDIENTS: WATER

DOSAGE AND ADMINISTRATION

USE AS BODY

WARNINGS

keep out of children

INACTIVE INGREDIENT

Aqua

INDICATIONS AND USAGE

Suitable for dry and dehydrated skin

keep out of children

PURPOSE

Moisturize the skin